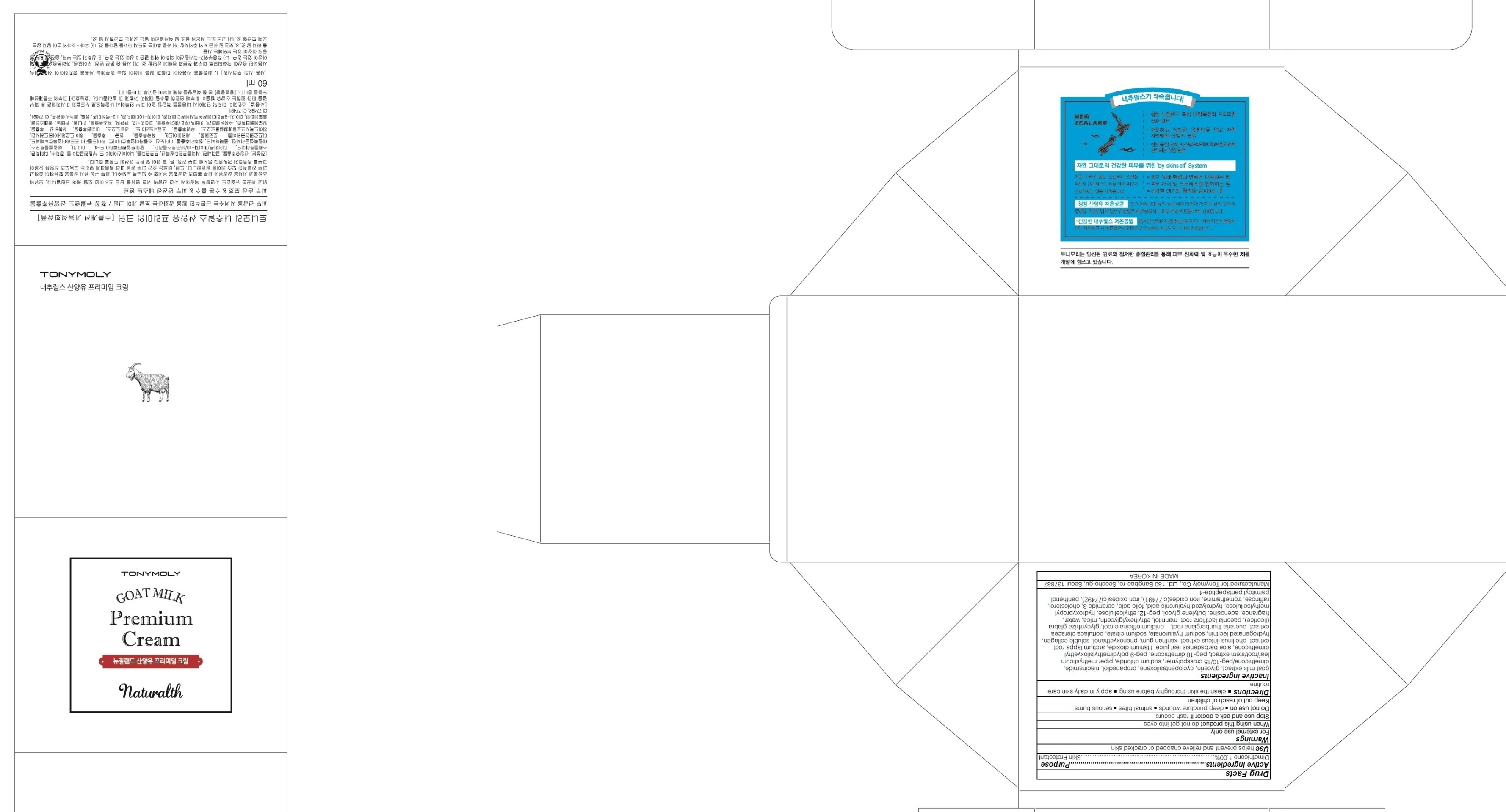 DRUG LABEL: TONYMOLY NATURALTH GOAT MILK PREMIUM
NDC: 59078-250 | Form: CREAM
Manufacturer: TONYMOLY CO.,LTD
Category: otc | Type: HUMAN OTC DRUG LABEL
Date: 20160120

ACTIVE INGREDIENTS: Dimethicone 0.6 g/60 mL
INACTIVE INGREDIENTS: goat milk; glycerin

ACTIVE INGREDIENT

Active ingredients: Dimethicone 1.00%

INACTIVE INGREDIENT

Inactive ingredients: goat milk extract, glycerin, cyclopentasiloxane, propanediol, niacinamide, dimethicone/peg-10/15 crosspolymer, sodium chloride, piper methysticum leaf/root/stem extract, peg-10 dimethicone, peg-9 polydimethylsiloxyethyl dimethicone, aloe barbadensis leaf juice, titanium dioxide, arctium lappa root extract, phellinus linteus extract, xanthan gum, phenoxyethanol, soluble collagen, hydrogenated lecithin, sodium hyaluronate, sodium citrate, portulaca oleracea extract, pueraria thunbergiana root, cnidium officinale root, glycyrrhiza glabra (licorice), paeonia lactiflora root, mannitol, ethylhexylglycerin, mica, water, fragrance, adenosine, butylene glycol, peg-12, ethylcellulose, hydroxypropyl methylcellulose, hydrolyzed hyaluronic acid, folic acid, ceramide 3, cholesterol, raffinose, tromethamine, iron oxides(ci77491), iron oxides(ci77492), panthenol, palmitoyl pentapeptide-4

PURPOSE

Purpose: Skin Protectant

WARNINGS

Warnings: For external use only

When using this product do not get into eyes

Stop use and ask a doctor if rash occurs

Do not use on - deep puncture wounds - animal bites - serious burns

Keep out of reach of children

KEEP OUT OF REACH OF CHILDREN

Use

Use: helps prevent and relieve chapped or cracked skin

Directions

Directions: - clean the skin thoroughly before using - apply in daily skin care routined